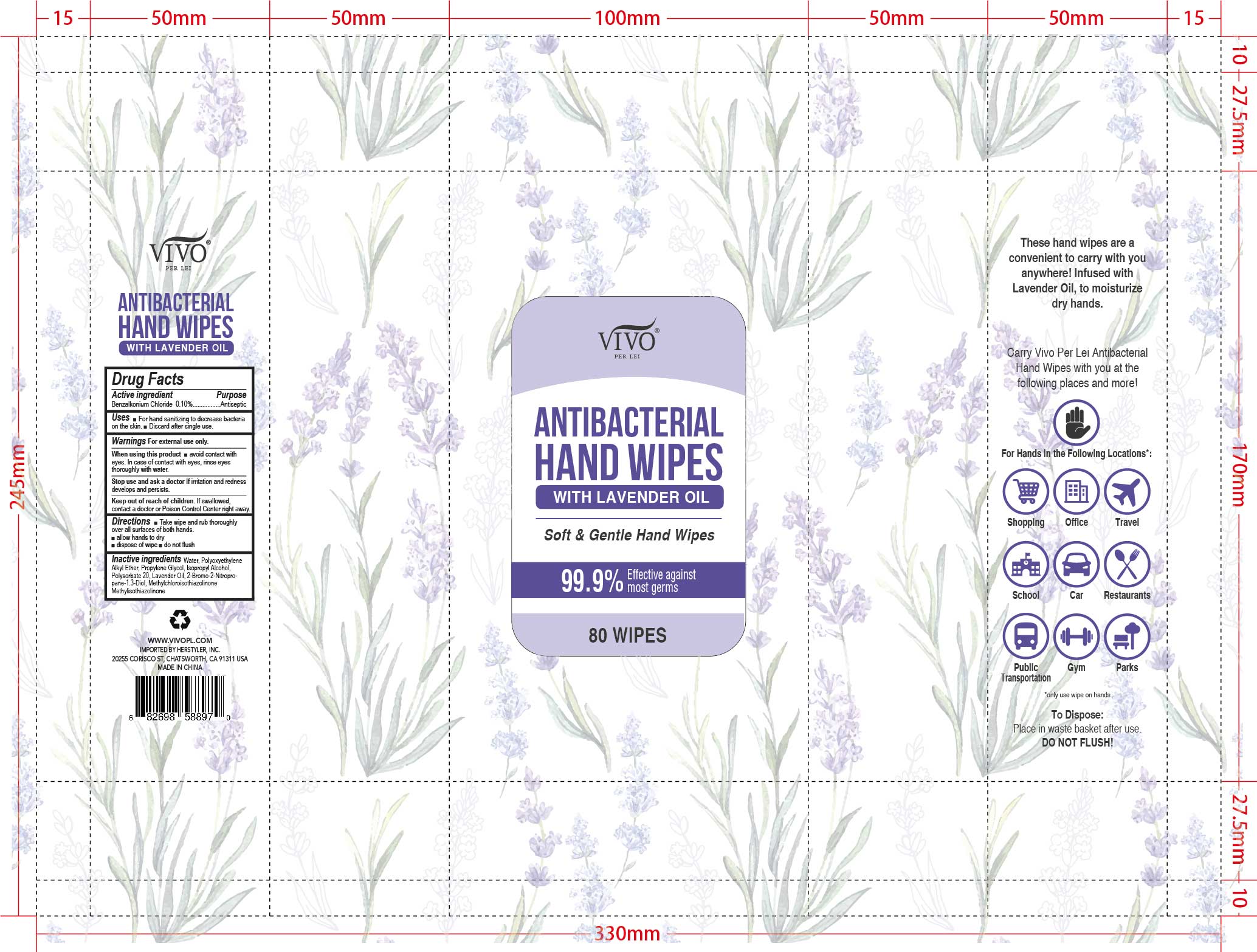 DRUG LABEL: VIVO ANTIBACTERIAL HAND WIPES

NDC: 75177-058 | Form: SOLUTION
Manufacturer: Herstyler, Inc.
Category: otc | Type: HUMAN OTC DRUG LABEL
Date: 20201004

ACTIVE INGREDIENTS: BENZALKONIUM CHLORIDE 3.375 mg/1 1
INACTIVE INGREDIENTS: WATER; PROPYLENE GLYCOL; ISOPROPYL ALCOHOL; POLYSORBATE 20; LAVENDER OIL; METHYLCHLOROISOTHIAZOLINONE; METHYLISOTHIAZOLINONE

75177_058 Vivo Lavender

Active Ingredient(s)

Benalkonium Chloride: 0.10%

Purpose

Antiseptic

Use

For hand sanitizing to decrease bacteria on the skin

Discard after single use

Warnings

For external use only.

When using this product, avoid contacting with eyes. In case of contact with eyes, rinse eyes thoroughly with water.

Stop use and ask a doctor if irritation or redness develops and persists

Keep out of reach of children. If swallowed, contact a doctor or a poison control center right away.

Directions

Take wipe and rub thoroughly over all surfaces of both hands

Allow hands to dry

Dispose of wipe

Do not flush

Inactive ingredients

Water, Polyoxyethlene Alkyl Ether, Propylene Glycol, Isopropyl Alcohol, Polysorbate 20, Lavender Oil, 2-Bromo-2-Nitropropane-1,3-diol, Methylchloroisothiazolinone, Methylisothiazolinone